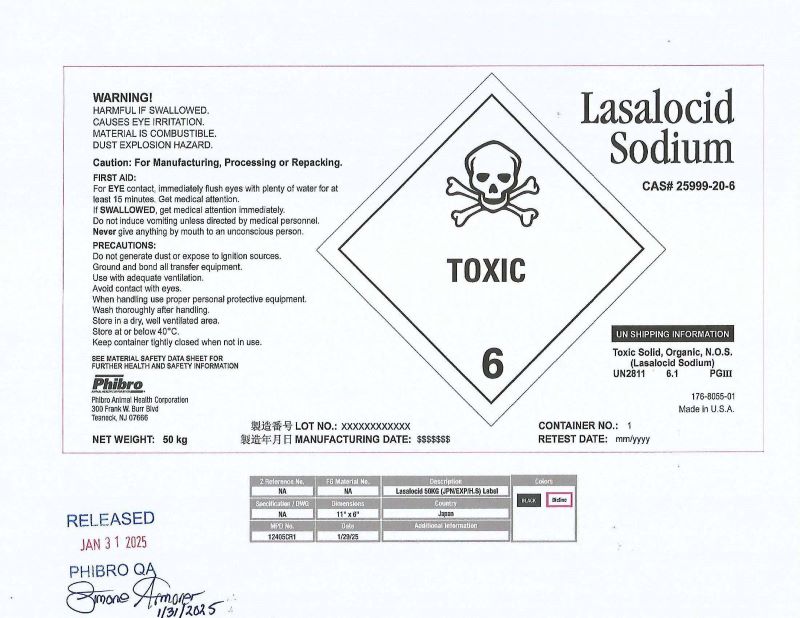 DRUG LABEL: Lasalocid Sodium
NDC: 66104-0402 | Form: POWDER
Manufacturer: Phibro Animal Health
Category: other | Type: BULK INGREDIENT - ANIMAL DRUG
Date: 20250918

ACTIVE INGREDIENTS: LASALOCID SODIUM 50 kg/50 kg

Lasalocid Sodim

WARNING

HARMFUL IF SWALLOWED.

CAUSES EYE IRRITATION.

MATERIAL IS COMBUSTIBLE.

DUST EXPLOSION HAZARD.

CAUTION: For Manufacturing, Processing or Repacking

FIRST AID:

For EYE contact, immediatedly flush eyes with plenty of water for at least 15 minutes. Get medicat attention.

If SWALLOWED, get medical attention immediately. Do not induce vomiting unless directed by medical personnel. Never give anything by mouth to an unconscious person.

PRECAUTIONS:

Do not generate dust or excuse to ignition sources.

Ground and bond all transfer equipment.

Use with adequate ventilation.

Avoid contact with eyes.

When handling use proper personal protective equipment.

Wash thoroughly after handling.

Store in a dry, well ventilated area.

Store at or below 40°C.

Keep container tightly closed when not in use.

SEE MATERIAL SAFETY DATA SHEET FOR FURTHER HEALTH AND SAFETY INFORMATION

Label

Lasalocid Sodium
CAS #25999-20-6
TOXIC
Phibro Animal Health Corporation
300 Frank W. Burr Blvd
Teaneck, NJ 07666
NET WEIGHT: 50 kg
LOT NO.: XXXXXXXXXXX
MANUFACTURING DATE: $$$$$$$
CONTAINER NO.: 1
RETEST DATE: mm/yyyy
UN SHIPPING INFORMATION
Toxic Solid, Organic, N.O.S.
(Lasalocid Sodium)
UN2811 6.1 PGIII
176-8055-01
Made in U.S.A.